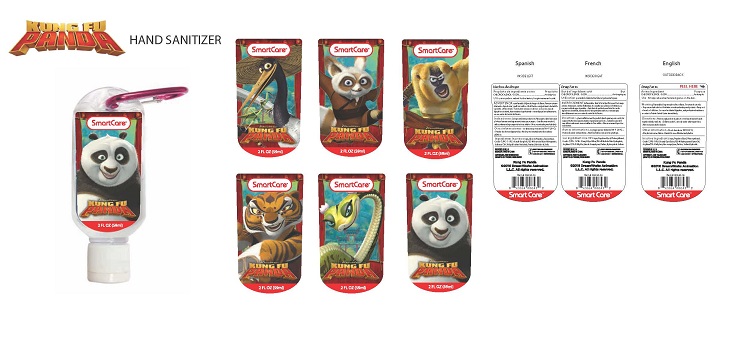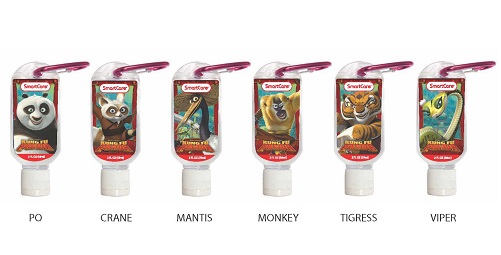 DRUG LABEL: Kung Fu Panda Hand Sanitizer
NDC: 70108-004 | Form: GEL
Manufacturer: Ashtel Studios Inc.
Category: otc | Type: HUMAN OTC DRUG LABEL
Date: 20191231

ACTIVE INGREDIENTS: CHLOROXYLENOL 0.05 g/59 g
INACTIVE INGREDIENTS: SODIUM HYDROXIDE; WATER; PROPYLENE GLYCOL; COCETH-7 CARBOXYLIC ACID; CHLOROPROPYLATE; PEG-40 CASTOR OIL; PPG-1-PEG-9 LAURYL GLYCOL ETHER; PHENOXYETHANOL

Kung Fu Panda Hand Sanitizer

Active Ingredient

Chloroxylenol 0.05%

Purpose: Antibacterial

Use

To decrease bacteria on the skin that could cause disease.

Keep out of reach of children.

INDICATIONS AND USAGE

Kung Fu Panda Hand Sanitizer

2 FL OZ (59mL)

Warnings

- for external use only-hands.
- keep out of eyes. avoid contact with broken skin.
- stop use and ask a Doctor if irritation or redness develops.
- do not inhale or ingest. if swallowed, get medical help or contact a poison control center right away.

Directions

- Rub a dime sized drop into hands.
- For children under 6 use under adult supervision.

Inactive Ingredients

water (aqua/eau), coceth-7, PPG-1-PEG-9 lauryl glycol ether, triethanolamine, PEG-40 hydrogenated castor oil, chloropropylate, fragrance (parfum).